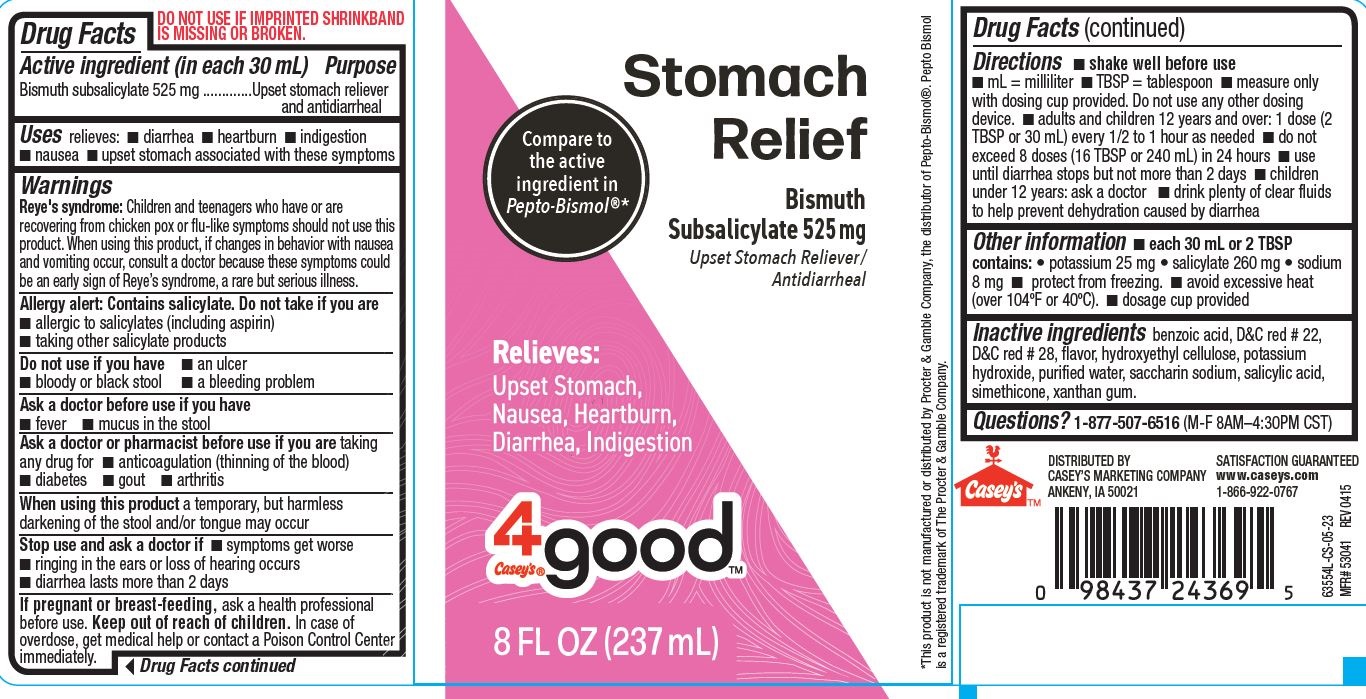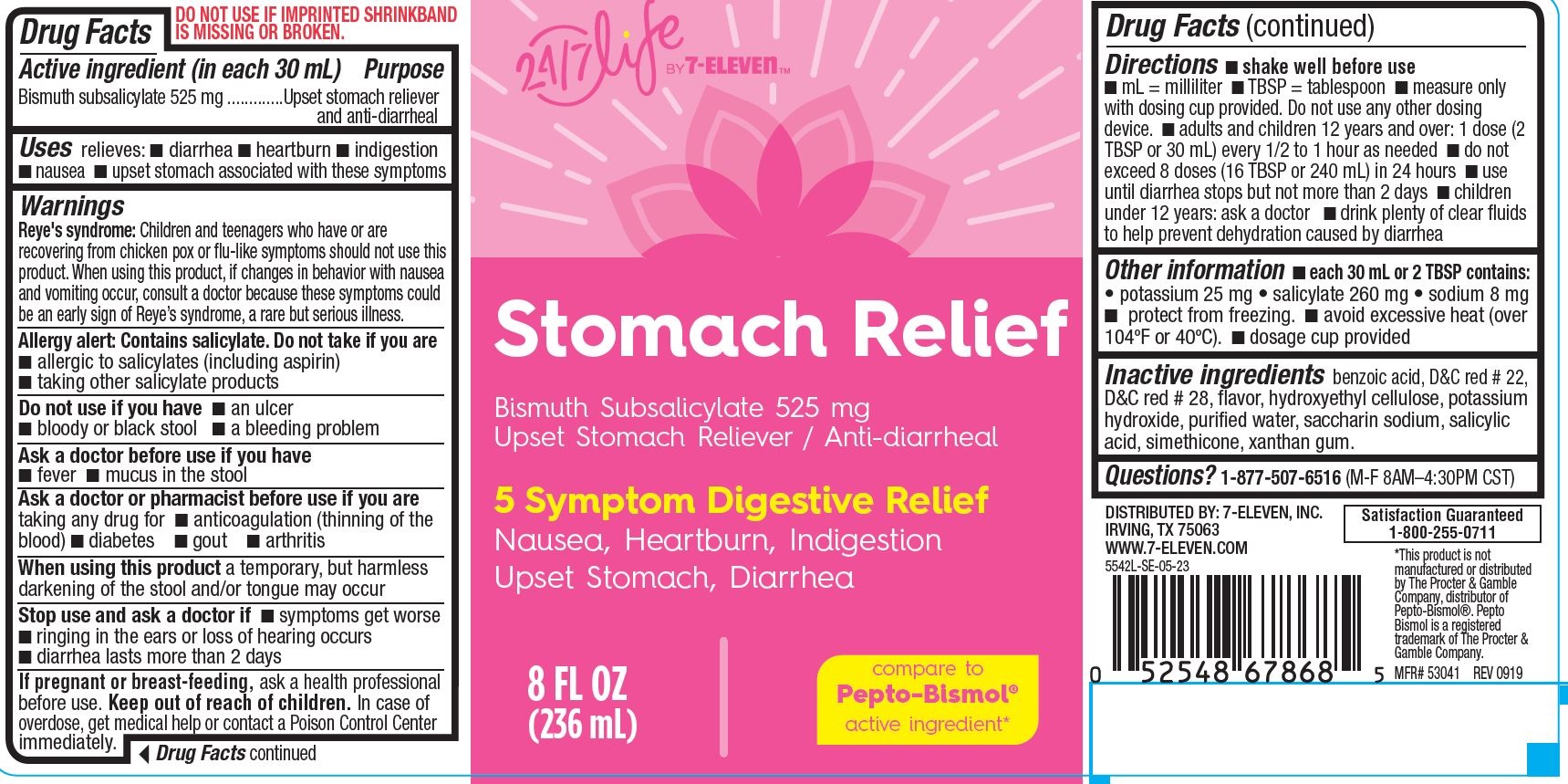 DRUG LABEL: Stomach Relief, 24-7 Life
NDC: 66715-8554 | Form: LIQUID
Manufacturer: Lil' Drug Store Products, Inc.
Category: otc | Type: HUMAN OTC DRUG LABEL
Date: 20241216

ACTIVE INGREDIENTS: BISMUTH SUBSALICYLATE 525 mg/30 mL
INACTIVE INGREDIENTS: HYDROXYETHYL CELLULOSE (2000 CPS AT 1%); SACCHARIN SODIUM; DIMETHICONE; WATER; XANTHAN GUM; SALICYLIC ACID; D&C RED NO. 22; D&C RED NO. 28; BENZOIC ACID; POTASSIUM HYDROXIDE

Stomach Relief, 8oz

Drug Facts

Active ingredient

Active ingredient (in each 30 mL)

Bismuth subsalicylate 525 mg

Purpose

Upset stomach reliever and antidiarrheal

Uses

Uses relieves:

- diarrhea
- heartburn
- indigestion
- nausea
- upset stomach associated with these symptoms

Warnings

Reye's syndrome

Children and teenagers who have or are recovering from chicken pox or flu-like symptoms should not use this product. When using this product, if changes in behavior with nausea and vomiting occur, consult a doctor because these symptoms could be an early sign of Reye’s syndrome, a rare but serious illness.

Allergy alert

Allergy alert: Contains salicylate. Do not take if you are

- allergic to salicylates (including aspirin)
- taking other salicylate products

Do not use if you have

- an ulcer
- bloody or black stool
- a bleeding problem

Ask a doctor or pharmacist before use if you are taking any drug for

- anticoagulation (thinning of the blood)
- diabetes
- gout
- arthritis

When using this product a temporary, but harmless darkening of the stool and/or tongue may occur

Stop use and ask a doctor if

- symptoms get worse
- ringing in the ears or loss of hearing occurs
- diarrhea lasts more than 2 days

If pregnant or breast-feeding, ask a health professional before use.

Keep out of reach of children. In case of overdose, get medical help or contact a Poison Control Center immediately.

Directions

- shake well before use
- mL = milliliter
- TBSP = tablespoon
- measure only with dosing cup provided. Do not use any other dosing device.
- adults and children 12 years and over: 1 dose (2 TBSP or 30 mL) every 1/2 to 1 hour as needed
- do not exceed 8 doses (16 TBSP or 240 mL) in 24 hours
- use until diarrhea stops but not more than 2 days
- children under 12 years: ask a doctor
- drink plenty of clear fluids to help prevent dehydration caused by diarrhea

Other information

- each 30 mL or 2 TBSP contains: • potassium 25 mg • salicylate 260 mg • sodium 8 mg
- protect from freezing.
- avoid excessive heat (over 104ºF or 40ºC).
- dosage cup provided

Inactive ingredients

benzoic acid, D&C red # 22, D&C red # 28, flavor, hydroxyethyl cellulose, potassium hydroxide, purified water, saccharin sodium, salicylic acid, simethicone, xanthan gum.

Questions

Questions? 1-877-507-6516 (M-F 8AM–4:30PM CST)

Stomach Relief, Casey's 4good PDP/Package

Stomach Relief

Compare to the active ingredient in Pepto-Bismol*

Bismuth

Subsalicylate 525 mg

Upset Stomach Reliever/

Antidiarrheal

Relieves:

Upset Stomach,

Nausea, Heartburn,

Diarrhea, Indigestion

[Casey's 4good logo]

8 FL OZ (237 mL)

Stomach Relief, 24/7 Life BY 7-ELEVEN

24/7 Life BY 7-ELEVEN

Stomach Relief

Bismuth Subsalicylate 525 mg
Upset Stomach Reliever / Anti-diarrheal

5 Symptom Digestive Relief
Nausea, Heartburn, Indigestion
Upset Stomach, Diarrhea

8 FL OZ
(236 mL)

compare to
Pepto-Bismol®
active ingredient*